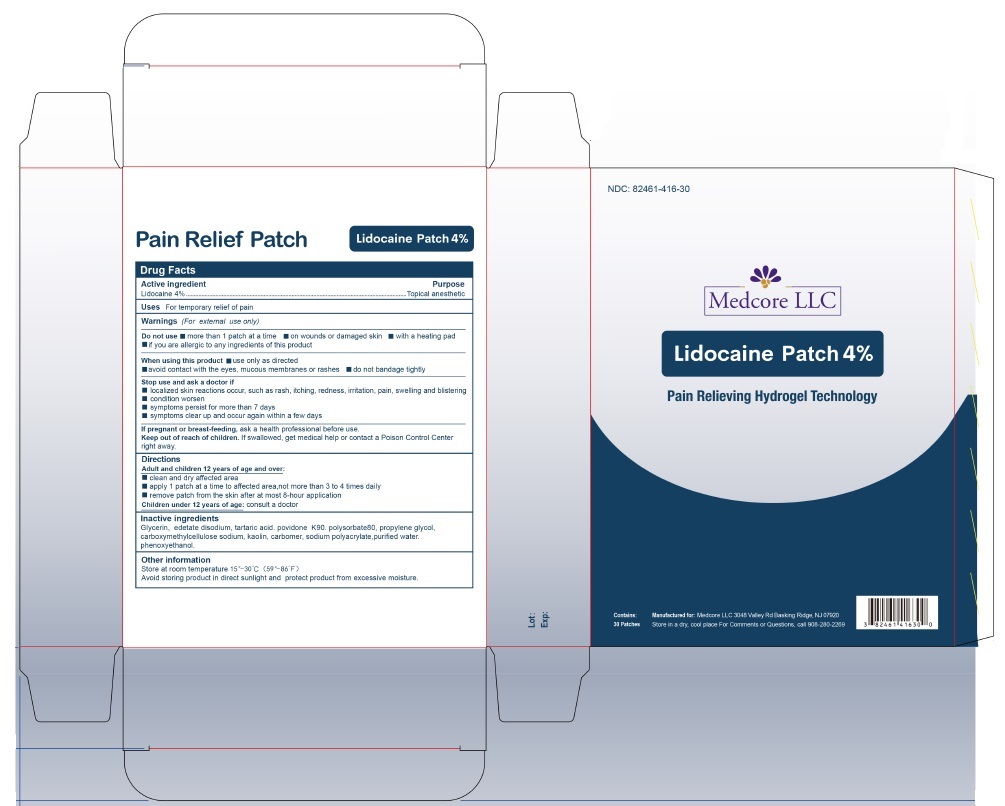 DRUG LABEL: Lidocaine Patch 4%
NDC: 82461-416 | Form: PATCH
Manufacturer: Medcore LLC
Category: otc | Type: HUMAN OTC DRUG LABEL
Date: 20250428

ACTIVE INGREDIENTS: LIDOCAINE 40 mg/1 g
INACTIVE INGREDIENTS: GLYCERIN; POLYSORBATE 80; PROPYLENE GLYCOL; POVIDONE, UNSPECIFIED; CARBOXYMETHYLCELLULOSE SODIUM, UNSPECIFIED; KAOLIN; SODIUM POLYACRYLATE (8000 MW); TARTARIC ACID; CARBOMER HOMOPOLYMER, UNSPECIFIED TYPE; EDETATE DISODIUM; WATER; METHYLPARABEN

Lidocaine Patch 4%

Drug Facts

Active ingredient

Lidocaine 4%

Purpose

Topical anesthetic

Uses

For temporary relief of pain

Warnings

(For external use only)

Do not use

- more than 1 patch at a time
- on wounds or damaged skin
- with a heating pad
- if you are allergic to any ingredients of this product

When using this product

- use only as directed
- avoid contact with the eyes, mucous membranes or rashes
- do not bandage tightly

Stop use and ask a doctor if

- localized skin reactions occur, such as rash, itching, redness, irritation, pain, swelling and blistering
- condition worsen
- symptoms persist for more than 7 days
- symptoms clear up and occur again within a few days

If pregnant or breast-feeding,

ask a health professional before use.

Keep out of reach of children.

If swallowed, get medical help or contact a Poison Control Center right away.

Directions

Adult and children 12 years of age and over:

- clean and dry affected area
- apply 1 patch at a time to affected area,not more than 3 to 4 times daily
- remove patch from the skin after at most 8-hour application

Children under 12 years of age: consult a doctor

Inactive ingredients

Glycerin, edetate disodium, tartaric acid. povidone K90. polysorbate80, propylene glycol, carboxymethylcellulose sodium, kaolin, carbomer, sodium polyacrylate,purified water. phenoxyethanol.

Other information

Store at room temperature 15°–30°C (59°–86°F)
Avoid storing product in direct sunlight and protect product from excessive moisture.

PRINCIPAL DISPLAY PANEL

NDC: 82461-416-30

Medcore LLC

Lidocaine Patch 4%

Pain Relieving Hydrogel Technology

Contains:

30 Patches

Manufactured for: Medcore LLC 3048 Valley Rd Basking Ridge, NJ 07920

Store in a dry, cool place for Comments or Questions, call 908-280-2269